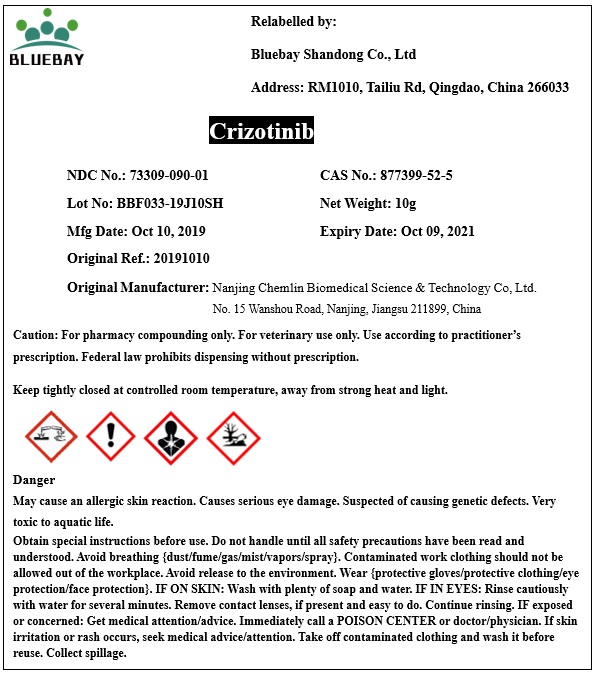 DRUG LABEL: Crizotinib
NDC: 73309-090 | Form: POWDER
Manufacturer: BLUEBAY SHANDONG CO.,LTD
Category: other | Type: BULK INGREDIENT
Date: 20200309

ACTIVE INGREDIENTS: CRIZOTINIB 1 g/1 g

Crizotinib